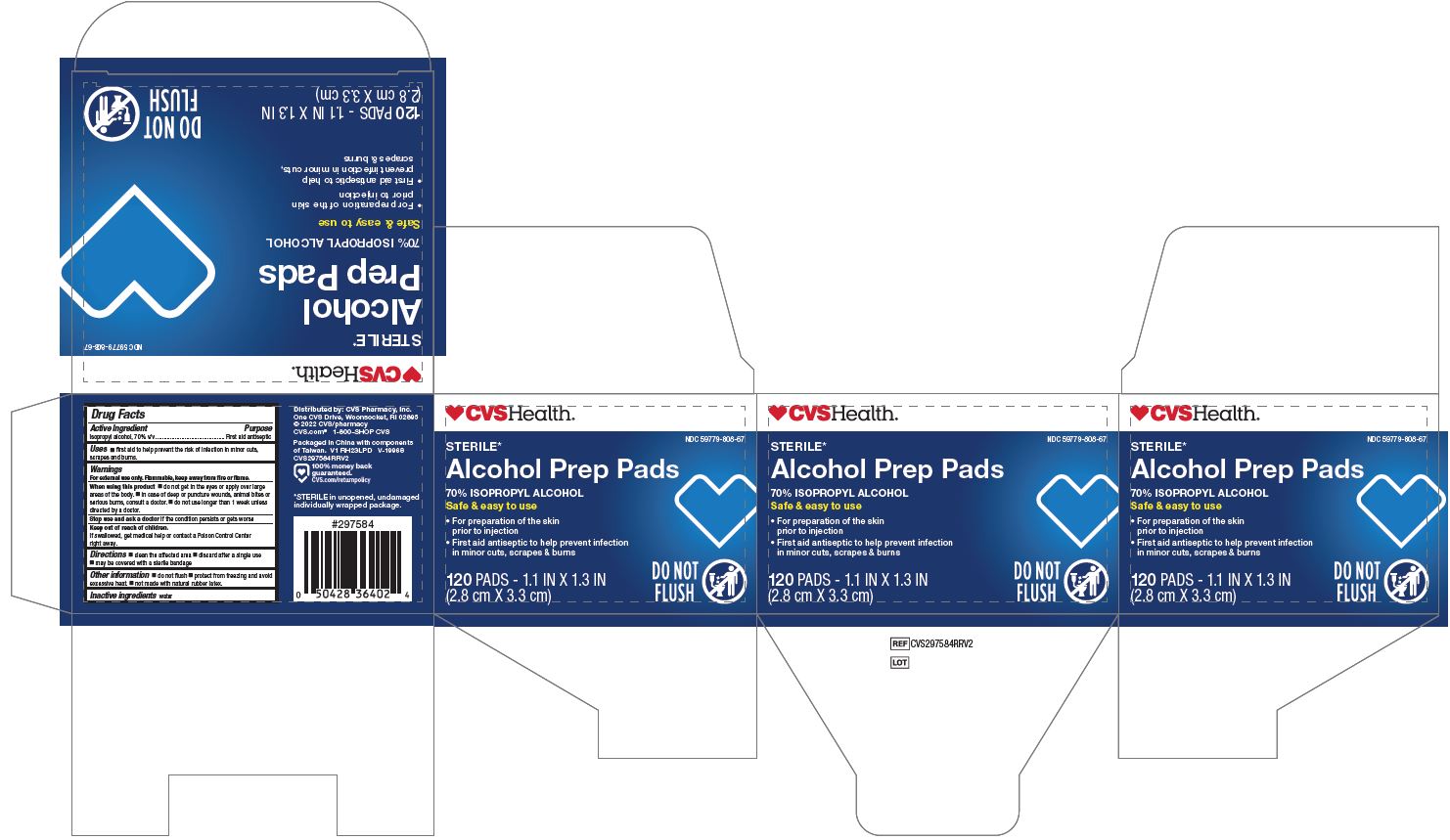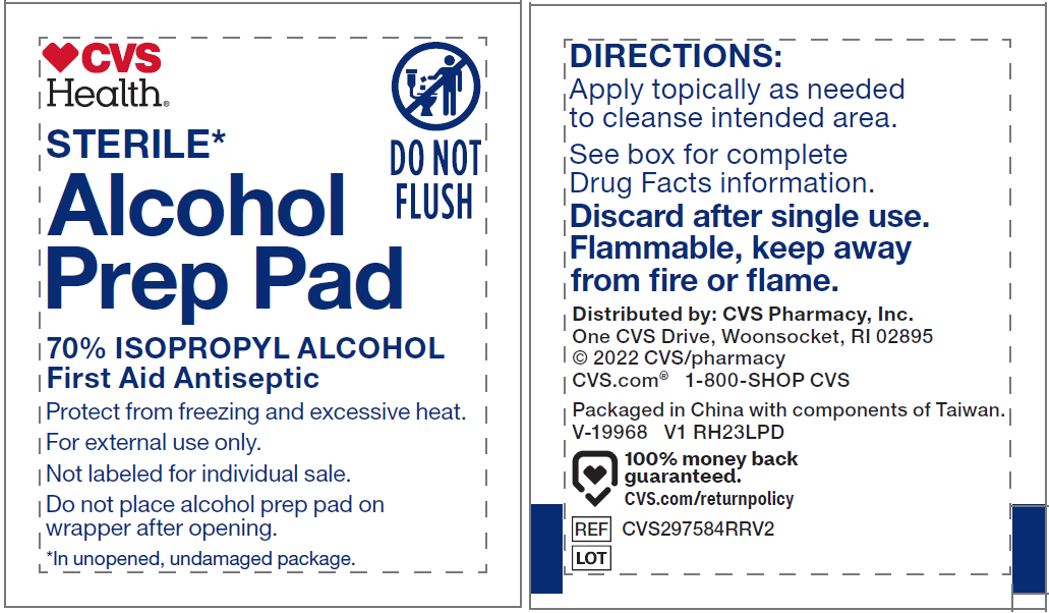 DRUG LABEL: CVS Alcohol Prep
NDC: 59779-808 | Form: SWAB
Manufacturer: CVS Pharmacy
Category: otc | Type: HUMAN OTC DRUG LABEL
Date: 20250103

ACTIVE INGREDIENTS: ISOPROPYL ALCOHOL 70 mL/100 mL
INACTIVE INGREDIENTS: WATER

59779-808 CVS IPA Swab

Active ingredient

Isopropyl alcohol 70% v/v

Purpose

first aid antiseptic

Uses

- first aid to help prevent the risk of infection in minor cuts, scrapes and burns

Warnings

- For external use only.
- Flammable, keep away from fire or flame.

Do not use

- • with electrocautery procedures
- • longer than 1 week unless directed by a doctor

When using this product

- • do not get into eyes
- • do not apply over large areas of the body
- • in case of deep or puncture wounds, animal bites or serious burns, consult a doctor

Stop use and ask a doctor if

- • irritation and redness develop
- • condition persists for more than 72 hours

Keep out of reach of children.

If accidentally swallowed, get medical help or contact a Poison Control Center right away.

Directions

- clean the affected area
- discard after single use
- may be covered with a sterile bandage

Other information

- do not flush
- protect from freezing, avoid excessive heat
- not made with natural rubber latex

Inactive ingredients

water

Manufacturing Information

Distributed by:

CVS Pharmacy, Inc.

One CVS Drive, Woonsocket, RI 02895

Made in China with components of Taiwan

1-800-SHOP CVS

CVS.com

REF: CVS97584RRV2

V1 RH23LPD